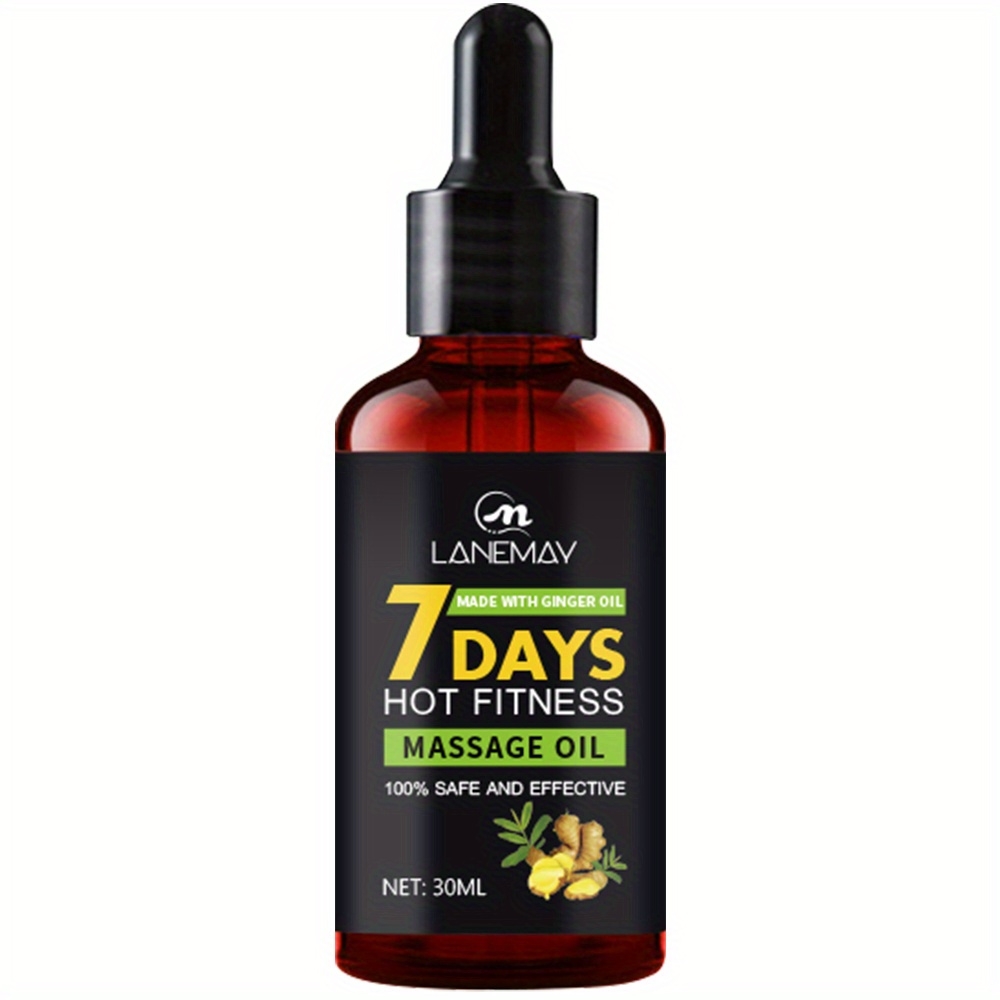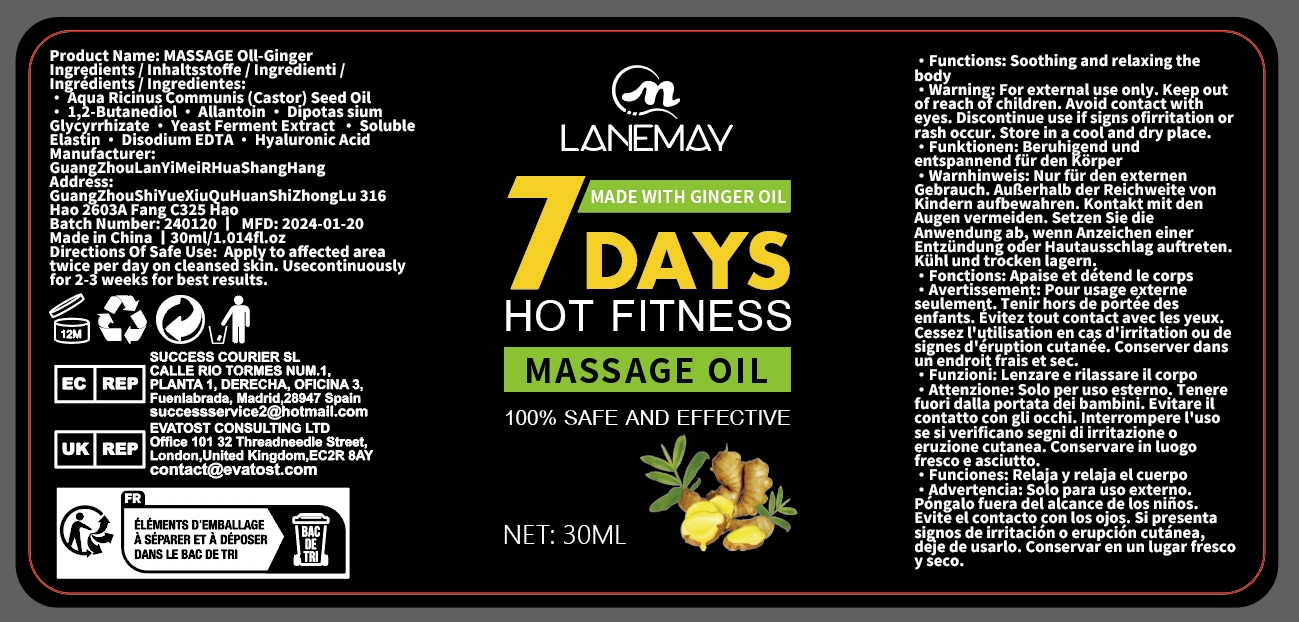 DRUG LABEL: Massage Oil
NDC: 84025-027 | Form: OIL
Manufacturer: Guangzhou Yanxi Biotechnology Co., Ltd
Category: otc | Type: HUMAN OTC DRUG LABEL
Date: 20240402

ACTIVE INGREDIENTS: 1,2-BUTANEDIOL 2 mg/20 mL
INACTIVE INGREDIENTS: WATER

DOSAGE AND ADMINISTRATION

use for body

WARNINGS

For external use only.

INACTIVE INGREDIENT

Aqua

INDICATIONS AND USAGE

Apply to affected area twice per day on cleansed skin.

Keep out of reach of children.

PURPOSE

Soothing and relaxing the body.